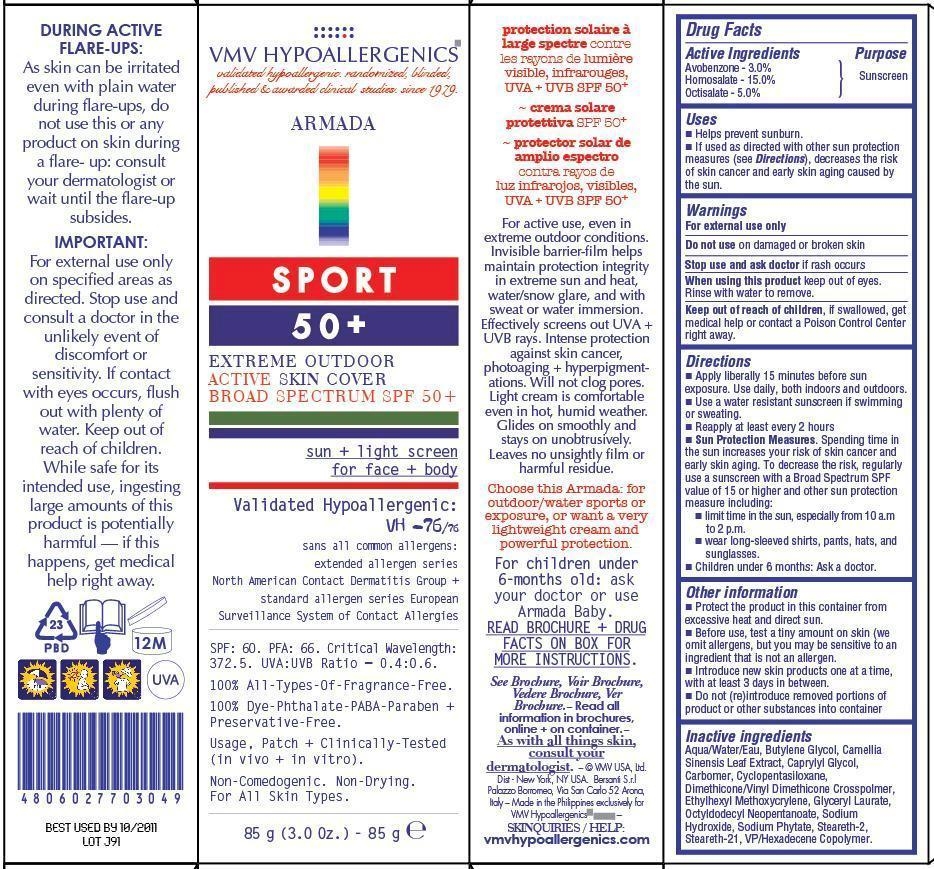 DRUG LABEL: VMV HYPOALLERGENICS ARMADA SPORT 50
NDC: 69774-008 | Form: CREAM
Manufacturer: SKIN SCIENCES LABORATORY INC.
Category: otc | Type: HUMAN OTC DRUG LABEL
Date: 20150428

ACTIVE INGREDIENTS: AVOBENZONE 3 g/85 g; HOMOSALATE 15 g/85 g; OCTISALATE 5 g/85 g
INACTIVE INGREDIENTS: WATER

Active Ingredients

Avobenzone

Homosalate

Octisalate

Uses

• Helps prevent sunburn
• If used as directed with other sun protection measures (see Direction), decrease the risk of skin cancer and early skin aging caused by the sun.

Warnings

For external use only
Do not use on damaged skin or broken skin
Stop use and ask doctor if rash occurs
When using this product keep out of eyes. Rinse with water to remove.

Directions

• Apply liberally 15 minutes before sun exposure. Use daily, both indoors and outdoors.
• Use water resistant sunscreen if swimming or sweating.
• Reapply at least every 2 hours.
• Sun Protection Measures. Spending time in the sun increases your risk of skin cancer and early skin aging. To decrease the risk, regularly use a sunscreen with a Broad Spectrum SPF value of 15 or higher and other sun protection measuring including:
• Limit time in the sun, especially from 10a.m. to 2 p.m.
• Wear long-sleeved shirt, pants, hats and sunglasses.
• Children under 6 months: Ask a doctor.

Other Information

• Protect the product in this container from excessive heat and direct sun.
• Before use, test a tiny amount on skin (we omit allergens, but you may be sensitive to an ingredient that is not an allergen).
• Introduce new skin products one at a time, with at least 3 days in between.
• Do not (re) introduce removed portions od product or other substances into container

Inactive Ingredients

Aqua/Water/Eau, Butylene Glycol, Camellia Sinensis Leaf Extract, Caprylyl Glycol, Carbomer, Cyclopentasiloxane, Dimethicone/Vinyl Dimethicone Crosspolymer, Ethylhexyl Methoxycrylene, Glyceryl Laurate, Octyldodecyl Neopentanoate, Sodium Hydroxide, Sodium Phytate, Steareth-2, Steareth-21, VP/Hexadecene Copolymer.

Purpose

Sunscreen

Important

Keep out of reach of children, if swallowed, get medical help or contact a Poison Control Center right away.

PRINCIPAL DISPLAY PANEL

VMV HYPOALLERGENICS

validated hypoallergenics. randomized, blinded,

published & awarded clinical studies. since 1979

Armada

SPORT

50+

EXTREME OUTDOOR

ACTIVE SKIN COVER

BROAD SPECTRUM SPF 50+

sun + light screen

for face + body

Validated Hypoallergenic: VH-76/76

sans all common allergens, extended

allergen seried: NACDG + ESSCA

SPF: 60. PFA: 66. Critical

Wavelength:372.5. UVA:UVB Ratio=

0.4:0.6. 100% All-Types-Of-

Fragrance-Free. 100% Dye-Phthalate-

PABA-Paraben + Preservative-Free.

Usage, Patch + Clinically-Tested

(in vivo + in vitro). Non-Drying.

Non-Comedogenic. For All Skin Types.

85G (3.0 Oz.) - 85g e

Active Ingredient with %

Active Ingredients

Avobenzone - 3.0%

Homosalate - 15.0%

Octisalate - 5.0%